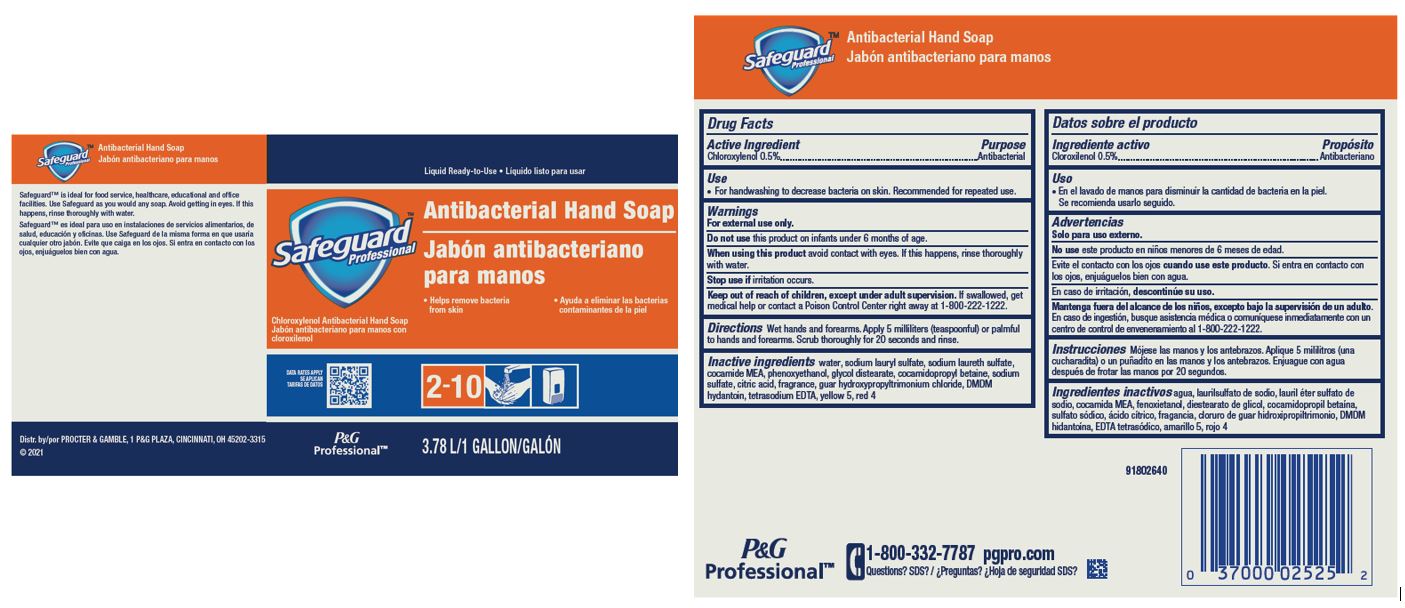 DRUG LABEL: Safeguard Antibacterial Hand
NDC: 69423-053 | Form: LIQUID
Manufacturer: The Procter & Gamble Manufacturing Company
Category: otc | Type: HUMAN OTC DRUG LABEL
Date: 20250317

ACTIVE INGREDIENTS: CHLOROXYLENOL 0.5 mg/100 mL
INACTIVE INGREDIENTS: PHENOXYETHANOL; TETRASODIUM EDTA; GUAR HYDROXYPROPYLTRIMONIUM CHLORIDE; WATER; SODIUM LAURYL SULFATE; SODIUM LAURETH SULFATE; COCAMIDE MEA; GLYCOL DISTEARATE; COCAMIDOPROPYL BETAINE; SODIUM SULFATE; CITRIC ACID; DMDM HYDANTOIN; YELLOW 5; RED 4

Safeguard™ Antibacterial Hand Soap

Drug Facts

Active Ingredient

Chloroxylenol 0.5%

Purpose

Antibacterial

Use

- For handwashing to decrease bacteria on skin. Recommended for repeated use.

Warnings

For external use only.

Do not use this product on infants under 6 months of age.

When using this product avoid contact with eyes. If this happens, rinse thoroughly with water.

Stop use if irritation occurs.

Keep out of reach of children, except under adult supervision. If swallowed, get medical help or contact a Poison Control Center right away.

Directions

Wet hands and forearms. Apply 5 milliliters (teaspoonful) or palmful to hands and forearms. Scrub thoroughly for 20 seconds and rinse.

Inactive ingredients

Water, sodium lauryl sulfate, sodium laureth sulfate, cocamide MEA, phenoxyethanol, glycol distearate, cocamidopropyl betaine, sodium sulfate, citric acid, fragrance, guar hydroxypropyltrimonium chloride, DMDM hydantoin, tetrasodium EDTA, yellow 5, red 4

Questions?

1-800-332-7787 (professional sizes)

1-800-595-1375 (personal size)

Distr. by PROCTER & GAMBLE, CINCINNATI, OH 45202.

PRINCIPAL DISPLAY PANEL - 3.78 L Bottle Label

Liquid Ready-to-Use

Safeguard™ Antibacterial Hand Soap

- Helps remove bacteria from skin

Chloroxylenol Antibacterial Hand Soap

3.78 L/1 GALLON